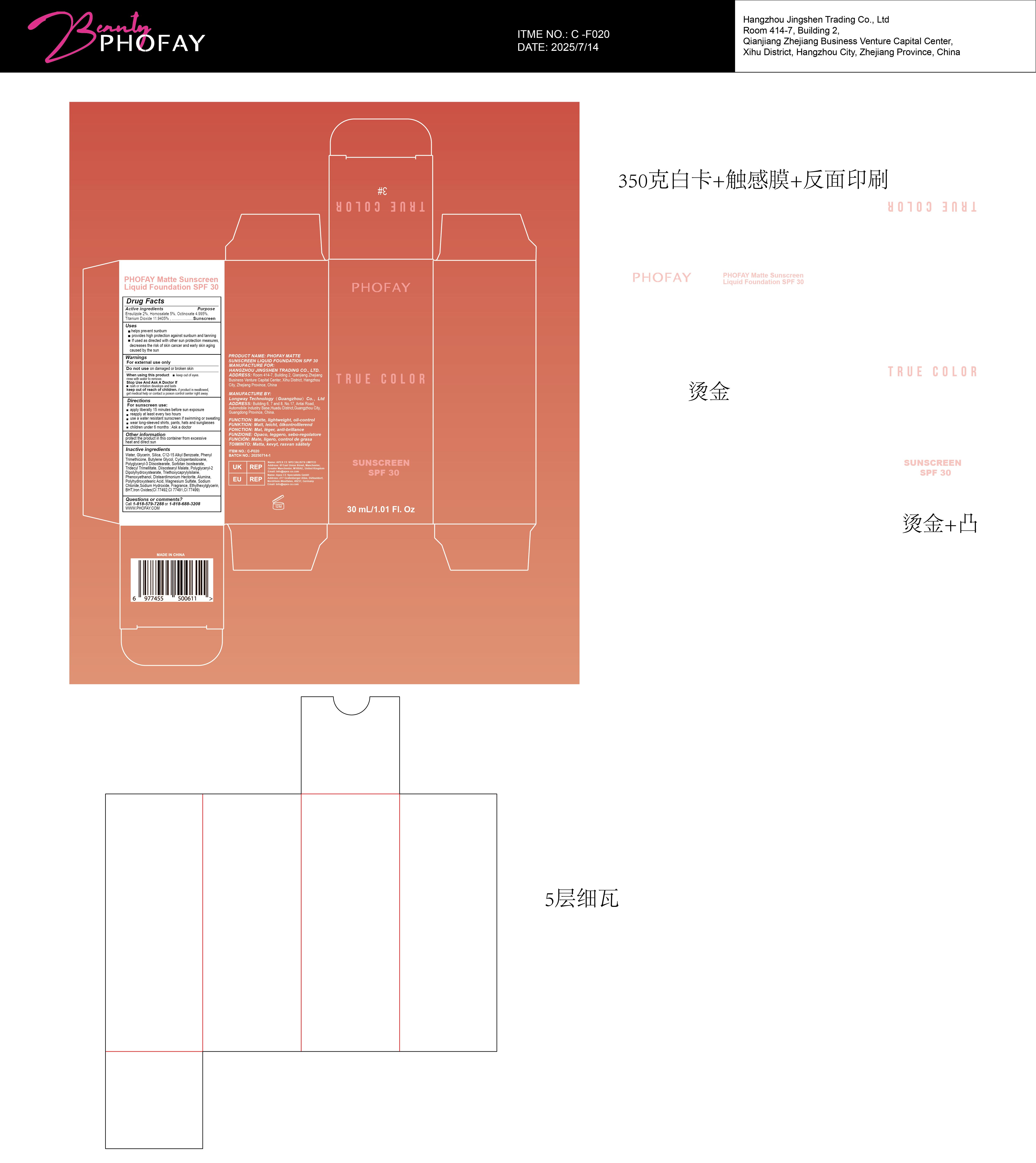 DRUG LABEL: PHOFAY Matte Sunscreen Liquid Foundation SPF 30 3
NDC: 87080-103 | Form: LOTION
Manufacturer: Hangzhou Jingshen Trading Co., Ltd.
Category: otc | Type: HUMAN OTC DRUG LABEL
Date: 20250827

ACTIVE INGREDIENTS: HOMOSALATE 0.05 g/1 g; TITANIUM DIOXIDE 0.119405 g/1 g; ENSULIZOLE 0.02 g/1 g; OCTINOXATE 0.04995 g/1 g
INACTIVE INGREDIENTS: GLYCERIN; PHENYL TRIMETHICONE; SORBITAN ISOSTEARATE; POLYGLYCERYL-2 DIPOLYHYDROXYSTEARATE; CI 77491; SODIUM CHLORIDE; TRIETHOXYCAPRYLYLSILANE; DISTEARDIMONIUM HECTORITE; SILICON DIOXIDE; POLYGLYCERYL-3 DIISOSTEARATE; TRIDECYL TRIMELLITATE; PHENOXYETHANOL; CYCLOPENTASILOXANE; ALUMINA; DIISOSTEARYL MALATE; CI 77492; POLYHYDROXYSTEARIC ACID (2300 MW); FRAGRANCE LEMON ORC2001060; ETHYLHEXYLGLYCERIN; C12-15 ALKYL BENZOATE; WATER; BUTYLENE GLYCOL; MAGNESIUM SULFATE; SODIUM HYDROXIDE; CI 77499; BHT

ACTIVE INGREDIENT

Ensulizole 2%,Homosalate 5%,Octinoxate 4.995%,Titanium Dioxide 11.9405%

KEEP OUT OF REACH OF CHILDREN

if product is swallowed,get medical help or contact a poison control center right away.

WARNINGS

For external use only

Do not use on damaged or broken skin

When using this product keep out of eyes.

rinse with water to remove.

Stop Use And Ask A Doctor lf

rash or irritation develops and lasts

keep out of reach of children.

if product is swallowed,get medical help or contact a poison control center right away.

DOSAGE AND ADMINISTRATION

For sunscreen use:
apply liberally 15 minutes before sun exposure

reapply at least every two hours

use a water resistant sunscreen if swimming or sweating

wear long-sleeved shirts, pants, hats and sunglasses

children under 6 months :Ask a doctor

INACTIVE INGREDIENT

Water, Glycerin, Silica, C12-15 Alkyl Benzoate, Phenyl Trimethicone, Butylene Glycol, Cyclopentasiloxane, Polyglyceryl-3 Diisostearate, Sorbitan Isostearate, Tridecyl Trimellitate, Diisostearyl Malate, Polyglyceryl-2 Dipolyhydroxystearate, Triethoxycaprylylsilane, Phenoxyethanol, Disteardimonium Hectorite, Alumina, Polyhydroxystearic Acid, Magnesium Sulfate, Sodium Chloride,Sodium Hydroxide, Fragrance, Ethylhexylglycerin,BHT,Iron Oxides(CI 77492,CI 77491,CI 77499)

OTHER SAFETY INFORMATION

if product is swallowed,get medical help or contact a poison control center right away.

PURPOSE

Sunscreen

INDICATIONS AND USAGE

For sunscreen use:
apply liberally 15 minutes before sun exposure

reapply at least every two hours

use a water resistant sunscreen if swimming or sweating

wear long-sleeved shirts, pants, hats and sunglasses

children under 6 months :Ask a doctor

QUESTIONS

Call 1-818-579-72880 or 1-818-688-3208
WWW.PHOFAY.COM